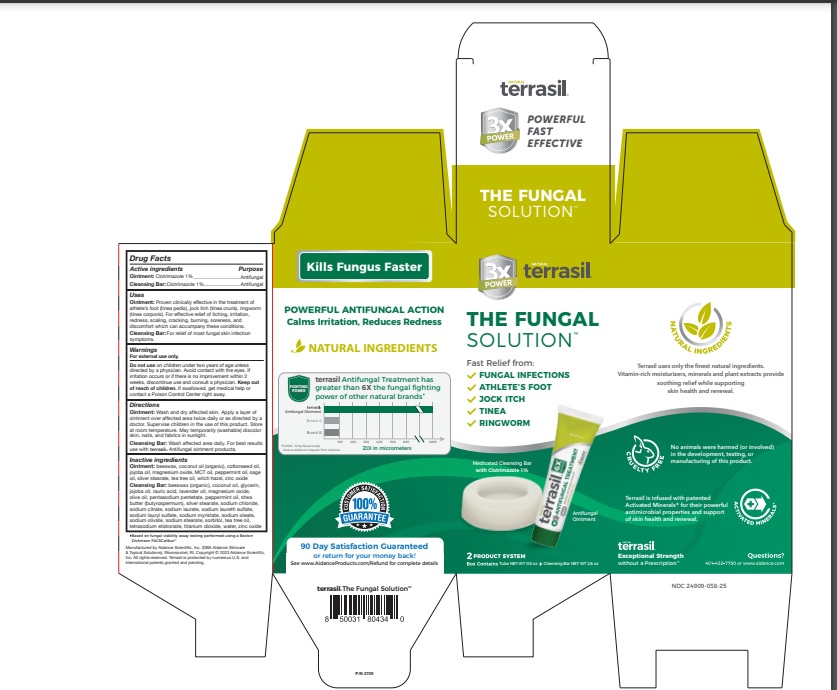 DRUG LABEL: terrasil The Fungal Solution Kit
NDC: 24909-038 | Form: KIT | Route: TOPICAL
Manufacturer: Aidance Scientific, Inc, DBA Aidance Skincare & Topical Solutions
Category: otc | Type: HUMAN OTC DRUG LABEL
Date: 20231108

ACTIVE INGREDIENTS: CLOTRIMAZOLE 1 g/100 g; CLOTRIMAZOLE 1 g/100 g
INACTIVE INGREDIENTS: YELLOW WAX; COCONUT OIL; COTTONSEED OIL; JOJOBA OIL; MAGNESIUM OXIDE; PALM OIL; PEPPERMINT OIL; SAGE OIL; SILVER STEARATE; TEA TREE OIL; WITCH HAZEL; ZINC OXIDE; YELLOW WAX; COCONUT OIL; JOJOBA OIL; GLYCERIN; LAURIC ACID; LAVENDER OIL; MAGNESIUM OXIDE; OLIVE OIL; PENTASODIUM PENTETATE; PEPPERMINT OIL; SHEA BUTTER; SODIUM CHLORIDE; SODIUM CITRATE; SODIUM LAURATE; SODIUM LAURETH SULFATE; SODIUM LAURYL SULFATE; SODIUM MYRISTATE; SODIUM OLEATE; SODIUM OLIVATE; SODIUM STEARATE; SORBITOL; TEA TREE OIL; ETIDRONATE TETRASODIUM; TITANIUM DIOXIDE; WATER; ZINC OXIDE; SILVER STEARATE

Drug Facts

Active Ingredient Purpose

Clotrimazole 1% Antifungal

Uses

Ointment: Proven clinically effective in the treatment of athlete’s foot (tinea pedis), jock itch (tinea cruris), ringworm (tinea corporis). For effective relief of itching, irritation, redness, scaling, cracking, burning, soreness, and discomfort which can accompany these conditions.

Cleansing Bar: For relief of most fungal skin infection symptoms.

Warnings

For external use only.
Do not useon children under two years of age unless directed by a physician. Avoid contact with the eyes. If irritation occurs or if there is no improvement within 2 weeks, discontinue use and consult a physician. Keep out of reach of children. If swallowed, get medical help or contact a Poison Control Center right away.

Directions

Ointment: Wash and dry affected skin. Apply a layer of ointment over affected area twice daily or as directed by a doctor. Supervise children in the use of this product.

Cleaning Bar: Wash affected area daily. For best results use with
terrasil® Antifungal ointment products.

Inactive Ingredients

Ointment: beeswax, coconut oil (organic), cottonseed oil, jojoba oil, magnesium oxide, MCT oil, peppermint oil, sage oil, silver stearate, tea tree oil, witch hazel, zinc oxide

Cleansing Bar: beeswax (organic), coconut oil, glycerin, jojoba oil, lauric acid, lavender oil, magnesium oxide, olive oil, pentasodium pentetate, peppermint oil, shea butter (butyrospermum), silver stearate, sodium chloride, sodium citrate, sodium laurate, sodium laureth sulfate, sodium lauryl sulfate, sodium myristate, sodium oleate, sodium olivate, sodium stearate, sorbitol, tea tree oil, tetrasodium etidronate, titanium dioxide, water, zinc oxide

Other information

Store at room temperature. May temporarily (washable) discolor skin and fabrics in sunlight.